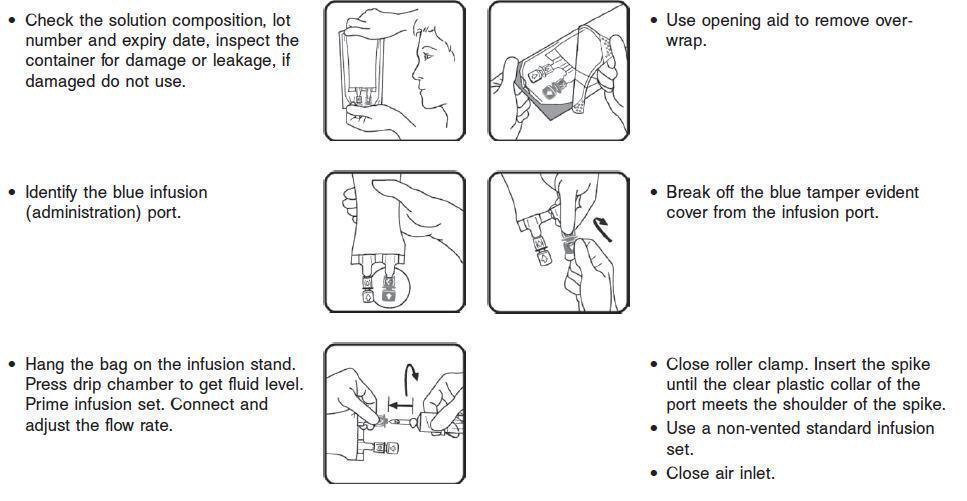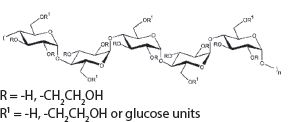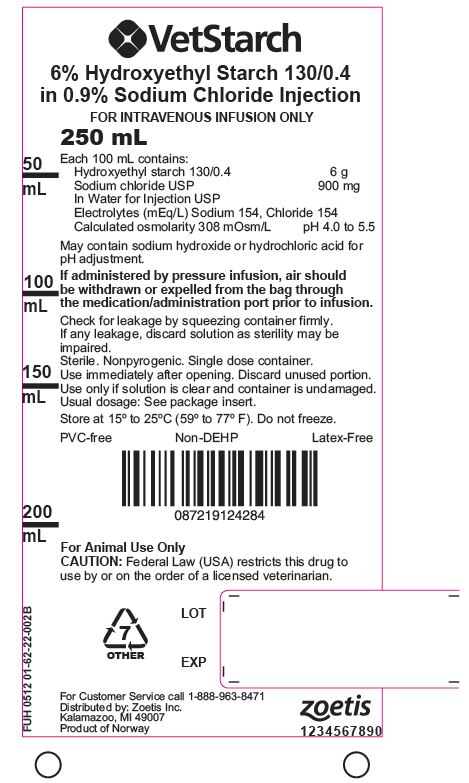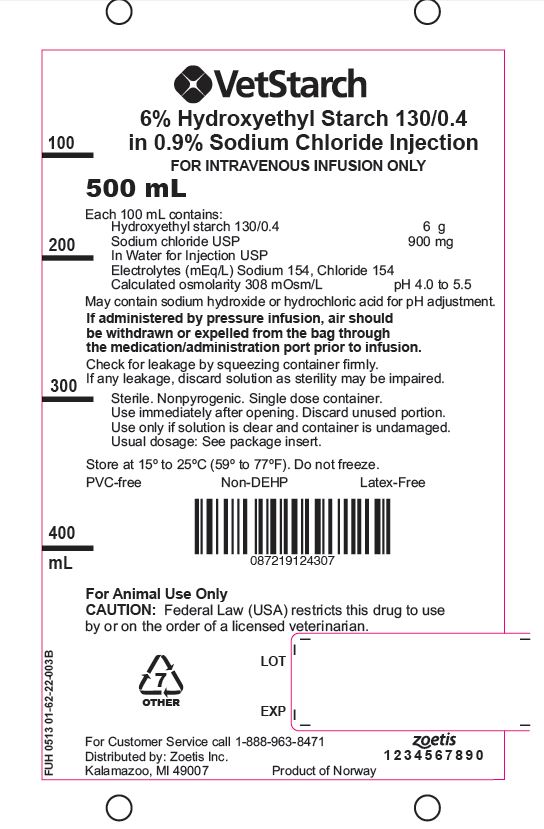 DRUG LABEL: VetStarch
NDC: 54771-4950 | Form: INJECTION, SOLUTION
Manufacturer: Zoetis Inc.
Category: animal | Type: PRESCRIPTION ANIMAL DRUG LABEL
Date: 20160715

ACTIVE INGREDIENTS: HYDROXYETHYL STARCH 130/0.4 6000 mg/100 mL
INACTIVE INGREDIENTS: SODIUM CHLORIDE 900 mg/100 mL; SODIUM HYDROXIDE; HYDROCHLORIC ACID

VetStarch ™
6% HYDROXYETHYL STARCH 130/0.4 IN 0.9% SODIUM CHLORIDE INJECTION

CAUTION:
Federal Law (USA) restricts this drug to use by or on the order of a licensed veterinarian.

HIGHLIGHTS OF PRESCRIBING INFORMATION:

These highlights do not include all of the information needed to use VetStarch safely and effectively. See full prescribing information for VetStarch.

VetStarch™
(6% HYDROXYETHYL STARCH 130/0.4 IN 0.9% SODIUM CHLORIDE INJECTION)
For administration by intravenous infusion.

INDICATIONS AND USAGE:
VetStarch is a plasma volume substitute indicated for the treatment and prophylaxis of hypovolemia.

DOSAGE AND ADMINISTRATION:
Administer by intravenous infusion only.
•Daily dose and rate of infusion depend on the patient's blood loss, hemodynamics and on the hemodilution effects
•Initiate infusion slowly due to possible anaphylactoid reactions

DOSAGE FORMS AND STRENGTHS:
250 ml and 500 ml flexible plastic intravenous solution containers. Each 100 ml contains 6 g hydroxyethyl starch 130/0.4 in Isotonic sodium chloride injection.

CONTRAINDICATIONS:
•Known hypersensitivity to hydroxyethyl starch
•Fluid overload e.g., pulmonary edema and congestive heart failure
•Renal failure with oliguria or anuria not related to hypovolemia
•Patients receiving dialysis
•Severe hypernatremia or severe hyperchloremia
•Intracranial bleeding

WARNINGS AND PRECAUTIONS:
•Anaphylactoid and hypersensitivity reactions
•Avoid fluid overload; adjust dosage in patients with cardiac or renal dysfunction
•In severe dehydration, a crystalloid solution should be given first
•Observe caution in patients with severe liver disease or bleeding disorders
•Monitor kidney function, fluid balance and serum electrolytes
•In humans elevated serum amylase values may occur and interfere with the diagnosis of pancreatitis
•High dosages may cause dilution of blood components

ADVERSE REACTIONS:
•Anaphylactoid/hypersensitivity reactions can occur. Most common adverse reactions ar pruritus, hemodilution (resulting in dilution of blood components, e.g., coagulation factors and other plasma proteins, and in a decrease in hematocrit).

To report SUSPECTED ADVERSE REACTIONS, call Zoetis Inc. at 1-888-963-8471.

DRUG INTERACTIONS:
No interactions with other drugs or nutritional products are known.
The safety and compatibility of additives have not been established.

USE IN SPECIFIC POPULATIONS:
Renal impaired: Use care in dosage selection.

After reviewing the Highlights Section, please read the following full prescribing information for this drug.

Revised: July 2015

01-59-22-002C

FULL PRESCRIBING INFORMATION: CONTENTS

1. INDICATIONS AND USAGE

2. DOSAGE AND ADMINISTRATION
2.1 Adult Dose
2.2 Directions for Use of VetStarch™

3. DOSAGE FORMS AND STRENGTHS

4. CONTRAINDICATIONS

5. WARNINGS AND PRECAUTIONS
5.1 General Warnings and Precautions
5.2 Monitoring: Laboratory Tests
5.3 Interference with Laboratory Tests

6. ADVERSE REACTIONS
6.1 Overall Adverse Reaction Profile

7. DRUG INTERACTIONS

8. USE IN SPECIFIC POPULATIONS
8.1 Pregnancy
8.2 Labor and Delivery
8.3 Renal Impairment

9. OVERDOSAGE

10. DESCRIPTION

11. CLINICAL PHARMACOLOGY
11.1 Mechanism of Action

12. NONCLINICAL TOXICOLOGY
12.1 Carcinogenesis, Mutagenesis, Impairment of Fertility
12.2 Animal Toxicology and Pharmacology
12.2.1 Toxicology
12.2.2 Pharmacology

13. REFERENCES

14. HOW SUPPLIED / STORAGE AND HANDLING

FULL PRESCRIBING INFORMATION

For Animal Use Only
CAUTION: Federal Law (USA) restricts this drug to use by or on the order of a licensed veterinarian.

1. INDICATIONS AND USAGE

VetStarch™ (6% hydroxyethyl starch 130/0.4 in 0.9% sodium chloride injection) is indicated for the treatment and prophylaxis of hypovolemia. It is not a substitute for red blood cells or coagulation factors in plasma.

2. DOSAGE AND ADMINISTRATION

VetStarch is administered by intravenous infusion only. The daily dose and rate of infusion depend on the patient’s blood loss, on the maintenance or restoration of hemodynamics and on the hemodilution (dilution effect). VetStarch can be administered repetitively over several days. [See Warnings and Precautions (5)]
The initial 10 to 20 mL should be infused slowly, keeping the patient under close observation due to possible anaphylactoid reactions. [see General Warnings and Precautions (5.1)]

2.1 Adult Dose

As a general recommendation, the class of synthetic colloids are prescribed at doses up to 20 mL per kg of body weight per day in small animal patients.1 In a 30 kg patient, this is a dose of 600 mL of VetStarch (equivalent to 1.2 g hydroxyethyl starch and 3.1 mEq sodium per kg of body weight). The use of 6% hydroxyethyl starch 130/0.4 has been dosed at 50 mL per kg of body weight per day in human studies.^2

2.2 Directions for Use of VetStarch

1. Do not remove the IV container from its overwrap until immediately before use.
2. Parenteral drug products should be inspected visually for particulate matter and discoloration prior to administration, whenever solution and container permit.
3. Do not administer unless the solution is clear, free from particles and the IV container is undamaged.
4. VetStarch should be used immediately after insertion of the administration set.
5. Do not vent.
6. If administered by pressure infusion, air should be withdrawn or expelled from the bag through the medication/administration port prior to infusion.
7. Discontinue the infusion if an adverse reaction occurs.
8. It is recommended that administration sets be changed at least once every 24 hours.
9. For single use only. Discard unused portion.

INCOMPATIBILITIES

The safety and compatibility of additives have not been established.

3. DOSAGE FORMS AND STRENGTHS

250 mL and 500 mL flexible plastic intravenous solution containers are available. Each 100 mL contains 6 g hydroxyethyl starch 130/0.4 in isotonic sodium chloride injection.

4. CONTRAINDICATIONS

The use of VetStarch™ is contraindicated in the following conditions:
• Known hypersensitivity to hydroxyethyl starch [see General Warnings and Precautions (5.1)]
• Fluid overload (hyperhydration) and especially in cases of pulmonary edema and congestive heart failure
• Renal failure with oliguria or anuria not related to hypovolemia
• Patients receiving dialysis treatment
• Severe hypernatremia or severe hyperchloremia
• Intracranial bleeding

5. WARNINGS AND PRECAUTIONS

5.1 General Warnings and Precautions

Anaphylactoid reactions (bradycardia, tachycardia, bronchospasm, non-cardiac pulmonary edema) have been reported with solutions containing hydroxyethyl starch.^3 If a hypersensitivity reaction occurs, administration of the drug should be discontinued immediately and the appropriate treatment and supportive measures should be undertaken until symptoms have resolved. [see Adverse Reactions (6)]
Fluid status and rate of infusion should be assessed regularly during treatment, especially in patients with cardiac insufficiency or severe kidney dysfunction.
In cases of severe dehydration, a crystalloid solution should be given first. Generally, sufficient fluid should be administered in order to avoid dehydration.
Caution should be observed before administering VetStarch to patients with severe liver disease or severe bleeding disorders. With the administration of certain hydroxyethyl starch solutions, disturbances of blood coagulation can occur depending on the dosage.^4,5

5.2 Monitoring: Laboratory Tests

Clinical evaluation and periodic laboratory determinations are necessary to monitor fluid balance, electrolyte concentrations, kidney function, acid-base balance, and coagulation parameters during prolonged parenteral therapy, or whenever the patient’s condition warrants such evaluation.

5.3 Interference with Laboratory Tests

In humans, elevated serum amylase levels may be observed temporarily following administration of the product and can interfere with the diagnosis of pancreatitis.
At high dosages the dilutional effects may result in decreased levels of coagulation factors and other plasma proteins and a decrease in hematocrit.^4,5

6. ADVERSE REACTIONS

6.1 Overall Adverse Reaction Profile

Products containing hydroxyethyl starch may lead to anaphylactoid reactions (hypersensitivity, mild influenza-like symptoms, bradycardia, tachycardia, bronchospasm, non-cardiac pulmonary edema). In the event of an intolerance reaction, the infusion should be discontinued immediately and the appropriate emergency medical treatment initiated. [see General Warnings and Precautions (5.1)]
Skin and subcutaneous tissue disorders in humans; prolonged administration of high dosages of hydroxyethyl starch may cause pruritus (itching) which is an undesirable effect observed with all hydroxyethyl starches.
Investigations; at high doses, the dilutional effects may result in decreased levels of coagulation factors and other plasma proteins, and a decrease in hematocrit. [see Interference with Laboratory Tests (5.3)]

7. DRUG INTERACTIONS

No interactions with other drugs or nutritional products are known. The safety and compatibility of other additives have not been established.^4,5 [see Directions for Use of VetStarch (2.2)]

8. USE IN SPECIFIC POPULATIONS

8.1 Pregnancy

The type of hydroxyethyl starch present in VetStarch had no teratogenic properties in rats or rabbits. At 5 g/kg of body weight per day, administered as a bolus injection, fetal retardations and embryolethal effects were observed in rats and rabbits, respectively.
In rats, a bolus injection of this dose during pregnancy and lactation reduced body weight of offspring and induced developmental delays. All adverse effects were seen exclusively at maternal toxic doses due to fluid overload. [see Toxicology (12.2.1)]
Fertility studies on directly exposed animals have not been conducted.

8.2 Labor and Delivery

Information on the use of VetStarch during labor or delivery is unknown.

8.3 Renal Impairment

VetStarch is mainly excreted by the kidneys, and the risk of adverse reactions to this drug may be greater in patients with impaired renal function. Volume status, infusion rate, and urine output should be closely monitored.

9. OVERDOSAGE

As with all plasma volume substitutes, overdosage can lead to overloading of the circulatory system (e.g., pulmonary edema). In this case, the infusion should be stopped immediately and, if necessary, a diuretic should be administered. [see General Warnings and Precautions (5.1)]

10. DESCRIPTION

VetStarch™ (6% hydroxyethyl starch 130/0.4 in 0.9% sodium chloride injection) is a clear to slightly opalescent, colorless to slightly yellow, sterile, non-pyrogenic, isotonic solution for intravenous administration using sterile equipment.

Each 100 mL of the solution contains:

Hydroxyethyl Starch 130/0.4 | 6 g
Sodium Chloride USP in Water for Injection USP | 900 mg
pH adjusted with Sodium Hydroxide USP or Hydrochloric Acid USP

Electrolytes (mEq/L): Sodium 154, Chloride 154, pH 4 to 5.5. Calculated osmolarity 308 mOsmol/L. The hydroxyethyl starch contained in VetStarch is a synthetic colloid for use in plasma volume replacement. The chemical name of hydroxyethyl starch is poly(O-2-hydroxyethyl) starch. The structural formula of hydroxyethyl starch is:

structure of Vetstarch

VetStarch is packaged in 250 mL and 500 mL flexible plastic containers made from coextruded polyolefin and is free of PVC, plasticizers, adhesives or latex (Non-DEHP, Latex-free). The container offers an air-closed system and can be used with nonvented IV sets which prevent external air contamination. The container is collapsible and can be used in emergency cases for pressure infusion.

11. CLINICAL PHARMACOLOGY

11.1 Mechanism of Action

VetStarch contains hydroxyethyl starch in a colloidal solution which expands plasma volume when administered intravenously. This effect depends on the mean molecular weight (130,000 daltons; range 110,000 – 150,000 daltons), the molar substitution by hydroxyethyl groups (0.4; range 0.38 – 0.45) on glucose units of the starch, the pattern of hydroxyethyl substitution (C2/C6 ratio) of approximately 9:1, and the concentration (6%), as well as the dosage and infusion rate.
Hydroxyethyl starch is a derivative of thin boiling waxy corn starch, which mainly consists of a glucose polymer (amylopectin) predominately composed of α-1-4-connected glucose units with several α-1-6-branches. Substitution of hydroxyethyl groups on the glucose units of the polymer reduces the normal degradation of amylopectin by α-amylase in the body. The low molar substitution (0.4) is the main pharmacological determinant for the beneficial effects of VetStarch on pharmacokinetics, intravascular volume and hemodilution.^6 To describe the molecular weight and molar substitution characteristics of the hydroxyethyl starch in VetStarch, the compound is designated as hydroxyethyl starch 130/0.4.

12. NONCLINICAL TOXICOLOGY

12.1 Carcinogenesis, Mutagenesis, Impairment of Fertility

Long-term studies in animals, to evaluate the carcinogenic potential of VetStarch, have not been performed. No mutagenic effects were observed with hydroxyethyl starch 130/0.4 10% solution in the following tests on mutagenic activity: Salmonella typhimurium reverse mutation assay (in vitro), mammalian cells in the in vitro gene mutation assay, assessment of the clastogenic activity in cultured human peripheral lymphocytes (in vitro), bone marrow cytogenetic test in Sprague-Dawley rats. Fertility studies on directly exposed animals have not been performed.

12.2.1 Toxicology

Three-month repeat infusion toxicology studies were conducted in rats and dogs in which three groups of animals were administered daily intravenous infusion over three hours. Dosing volumes of either 60 or 90 mL/kg body weight of hydroxyethyl starch 130/0.4 (10% solution), or 90 mL/kg 0.9% sodium chloride injection, were studied. Observed toxicity following repeat infusion of hydroxyethyl starch is consistent with the oncotic properties of the solution resulting in hypervolemia in the animals. There were no apparent gender-related effects on toxicity following repeat administration of hydroxyethyl starch 130/0.4 in rats or dogs.

In reproduction studies in rats and rabbits, hydroxyethyl starch 130/0.4 (10% solution) had no teratogenic properties. Embryolethal effects were observed in rabbits at 5 g/kg body weight/day. In rats, bolus injection of this dose during pregnancy and lactation reduced body weight of offspring and induced developmental delays. Signs of fluid overload were seen in the dams. Hydroxyethyl starch 130/0.4 (10% solution) was observed to have no effect in studies assessing skin sensitization, antigenicity, and blood compatibility.

12.2.2 Pharmacology

The pharmacodynamic effect of VetStarch™ was examined in a hemorrhagic shock model in conscious rats, and a hemodilution model in dogs. In both studies, the control group received pentastarch (6% hydroxyethyl starch 200/0.5).
VetStarch was as effective as pentastarch in maintaining cardiopulmonary function during isovolemic hemodilution in beagle dogs. In the three-hour follow-up period, no additional administration of colloid was necessary.
There were no differences in long-term survival of rats after a single administration of VetStarch and pentastarch solutions following induced hemorrhagic shock (67% and 50% blood loss). In the 67% induced bleeding group receiving VetStarch (N=6), the survival rate was 83% which is within the normal range for this type of experiment. In the corresponding pentastarch group, survival was 100%. Infusion of Ringer’s lactate resulted in a 50% survival rate after a 50% blood loss and a 0% survival after a 67% blood loss. After multiple intravenous infusions of 0.7 g per kg body weight per day of 10% hydroxyethyl starch 130/0.4, or 10% hydroxyethyl starch 200/0.5 solution, during 18 consecutive days, the plasma hydroxyethyl starch concentration in rats treated with hydroxyethyl starch 130/0.4 was lower compared to rats treated with hydroxyethyl starch 200/0.5. Hydroxyethyl starch 130/0.4 was eliminated faster than hydroxyethyl starch 200/0.5. In both groups, clear signs of hydroxyethyl starch tissue storage were detected in lymph nodes and spleen. Numerous empty vacuoles in macrophages were observed. Only minimal cellular vacuolization was found in the liver and kidney. Histochemical differences between the groups were not observed.

A study with 10% radiolabeled ^14C-hydroxyethyl starch 130/0.4 and 10% ^14C-hydroxyethyl starch 200/0.5 solutions was carried out.^7 In animals treated with hydroxyethyl starch 130/0.4, radioactivity decreased from 4.3% of the total administered dose (2.6 g hydroxyethyl starch 130/0.4 per animal) on day 3 to 0.65% on day 52. In animals treated with hydroxyethyl starch 200/0.5, the ^14C activity decreased from 7.7% of the total administered dose (2.7 g hydroxyethyl starch 200/0.5 per animal) on day 3 to 2.45% on day 52. These results confirm the faster elimination and lower persistence of hydroxyethyl starch 130/0.4 in tissue.

13. REFERENCES

1. Silverstein D, Hopper K. Small Animal Critical Care Medicine. (2009).
2. Neff T., Doelberg M., Jungheinrich C., Sauerland A., Spahn D., Stocker R., “Repetitive Large-Dose Infusion of the Novel Hydroxyethyl Starch 130/0.4 in Patients with Severe Head Injury.” Anesth Analg 96 (2003): 1453-9
3. DiBartola, S. Fluid, Electrolyte, & Acid-Base Disorders in Small Animal Practice. (2011).
4. Smiley, et al. “The Use of Hetastarch as Adjunct Therapy in 36 dogs with Hypoalbuminemia: a Phase Two Clinical Trial.”J Vet Intern Med, 8 (1994): 195-200.
5. Smart, et al. “The Effect of Hetastarch (670/0.75) In Vivo on Platelet Closure Time in the Dog.” J Vet Emerg Crit Care, 19(5) (2009): 444-449.
6. Jungheinrich, C., Neff, T. “Pharmacokinetics of hydroxyethyl starch.” Clin Pharmacokinetik 44 (7) (2005): 681-699.
7. Leuschner, J., Opitz, J., Winkler, A., Scharpf, R., Bepperling, F. “Tissue storage of 14C-labeled hydroxyethyl starch (HES) 130/0.4 and HES 200/0.5 after repeated intravenous administration to rats.” Drugs R D, 4 (6) (2003): 331-8.

14. HOW SUPPLIED / STORAGE AND HANDLING

VetStarch™ (6% hydroxyethyl starch 130/0.4 in 0.9% sodium chloride injection) for intravenous infusion is supplied in the following primary container and carton sizes:
Polyolefin bag with overwrap: 250 mL and 500 mL
Carton of 20 x 500 mL
Carton of 30 x 250 mL
Store at 15° to 25°C (59° to 77°F), Do not freeze

For Customer Service call 1-888-963-8471

Distributed by:

Zoetis Inc.

Kalamazoo, MI 49007

Product of Norway

PRINCIPAL DISPLAY PANEL 250 ml

VetStarch
6% Hydroxyethyl Starch 130/0.4 in 0.9% Sodium Chloride Injection
FOR INTRAVENOUS INFUSION ONLY
250 ml

VetStarch 250 mL label

PRINCIPAL DISPLAY PANEL 500 ML

VetStarch
6% Hydroxyethyl Starch 130/0.4 in 0.9% Sodium Chloride Injection
FOR INTRAVENOUS INFUSION ONLY
500 ml

VetStarch 500 mL Label